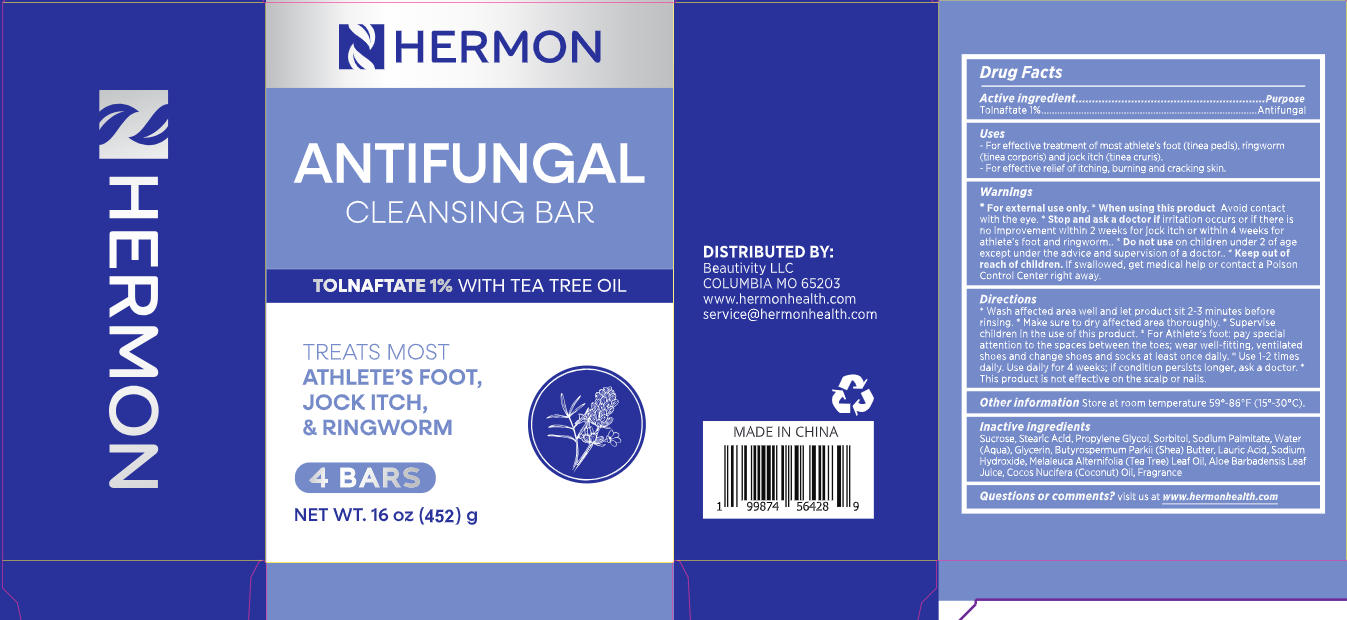 DRUG LABEL: Hermon Antifungal Soap. 4 packs
NDC: 85398-020 | Form: SOAP
Manufacturer: Beautivity LLC
Category: otc | Type: HUMAN OTC DRUG LABEL
Date: 20260118

ACTIVE INGREDIENTS: TOLNAFTATE 10 mg/1 g
INACTIVE INGREDIENTS: SODIUM PALMITATE; SUCROSE; COCOS NUCIFERA (COCONUT) OIL; LAURIC ACID; STEARIC ACID; GLYCERIN; PROPYLENE GLYCOL; SODIUM HYDROXIDE; AQUA; SORBITOL; MELALEUCA ALTERNIFOLIA (TEA TREE) LEAF OIL; ALOE BARBADENSIS LEAF JUICE; BUTYROSPERMUM PARKII (SHEA) BUTTER

85398-020-03 label

ACTIVE INGREDIENT

Tolnaftate 1%

PURPOSE

Antifungal

DOSAGE AND ADMINISTRATION

- For effective treatment of most athlete’s foot (tinea pedis), ringworm (tinea corporis) and jock itch (tinea cruris).
- For effective relief of itching, burning and cracking skin.

INDICATIONS AND USAGE

- Wash affected area well and let product sit 2–3 minutes before rinsing.
- Make sure to dry affected area thoroughly.
- Supervise children in the use of this product.
- For Athlete’s foot: pay special attention to the spaces between the toes; wear well-fitting, ventilated shoes and change shoes and socks at least once daily.
- Use 1–2 times daily. Use daily for 4 weeks; if condition persists longer, ask a doctor.
- This product is not effective on the scalp or nails.

WARNINGS

For external use only.

DO NOT USE

on children under 2 years of age unless directed by a doctor.

WHEN USING

avoide contact with eyes, lf contact occurs, rinse thoroughly with water.

STOP USE

Stop and ask a doctor if irritation occurs or if there is no improvement within 2 weeks for jock itch or within 4 weeks for athlete’s foot and ringworm.

KEEP OUT OF REACH OF CHILDREN

lf swallowed, get medical help orcontact a Poison Control Center right away.

INACTIVE INGREDIENT

(Original)
Sucrose, Stearic Acid, Propylene Glycol, Sorbitol, Sodium Palmitate, Water (Aqua), Glycerin, Butyrospermum Parkii (Shea) Butter, Lauric Acid, Sodium Hydroxide, Melaleuca Alternifolia (Tea Tree) Leaf Oil, Aloe Barbadensis Leaf Juice, Cocos Nucifera (Coconut) Oil
(Lavender)
Sucrose, Stearic Acid, Propylene Glycol, Sorbitol, Sodium Palmitate, Water (Aqua), Glycerin, Butyrospermum Parkii (Shea) Butter, Lauric Acid, Sodium Hydroxide, Melaleuca Alternifolia (Tea Tree) Leaf Oil, Aloe Barbadensis Leaf Juice, Cocos Nucifera (Coconut) Oil, Fragrance

STORAGE AND HANDLING

Store at room temperature 59°–86°F (15°–30°C).

QUESTIONS

visit us at www.hermonhealth.com